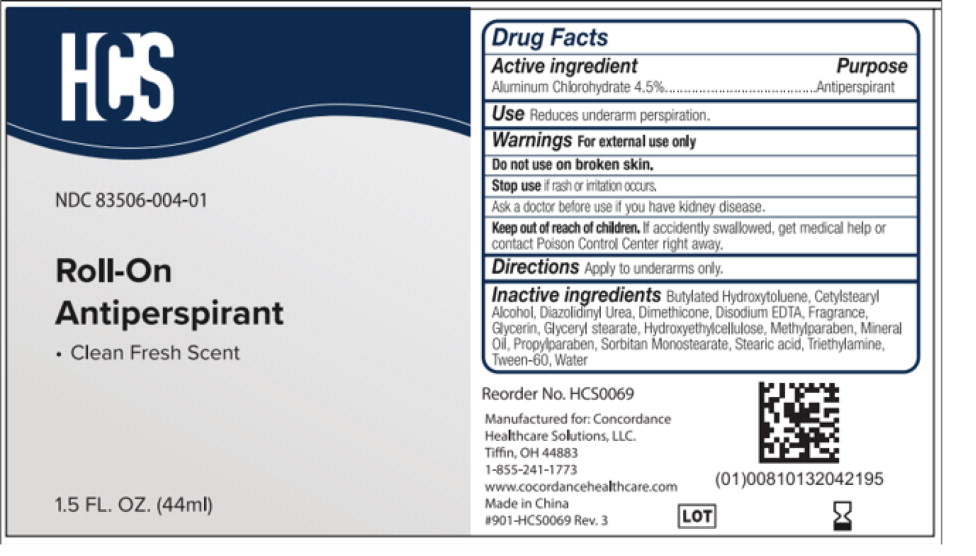 DRUG LABEL: HCS Roll-on Antiperspirant
NDC: 83506-004 | Form: LIQUID
Manufacturer: Concordance Healthcare Solutions, LLC.
Category: otc | Type: HUMAN OTC DRUG LABEL
Date: 20260112

ACTIVE INGREDIENTS: Aluminum Chlorohydrate 45 mg/1 mL
INACTIVE INGREDIENTS: Butylated Hydroxytoluene; Cetostearyl Alcohol; Diazolidinyl Urea; Dimethicone; Edetate Calcium Disodium; Fragrance Clean ORC0600327; Glycerin; Glyceryl 1-Stearate; Hydroxyethyl Cellulose, Unspecified; Methylparaben; Mineral Oil; Propylparaben; Sorbitan Monostearate; Stearic Acid; Triethylamine; Polysorbate 60; Water

Drug Facts

Active ingredient

Aluminum Chlorohydrate 4.5%

Purpose

Antiperspirant

Use

Reduces underarm perspiration.

Warnings

For external use only

Do not use on broken skin.

Stop use if rash or irritation occurs.

Ask a doctor before use if you have kidney disease.

Keep out of reach of children. If accidently swallowed, get medical help or contact Poison Control Center right away.

Directions

Apply to underarms only.

Inactive ingredients

Butylated Hydroxytoluene, Cetylstearyl Alcohol, Diazolidinyl Urea, Dimethicone, Disodium EDTA, Fragrance, Glycerin, Glyceryl stearate, Hydroxyethylcellulose, Methylparaben, Mineral Oil, Propylparaben, Sorbitan Monostearate. Stearic acid, Triethytamine, Tween-60, Water

Principal Display Panel – 1 Bottle

HCS

NDC 83506-004-01

Clean Fresh Scent
Roll-On
Antiperspirant/
Deodorant

- Fights Wetness & Odor

1.5 FL. OZ. (44ml)